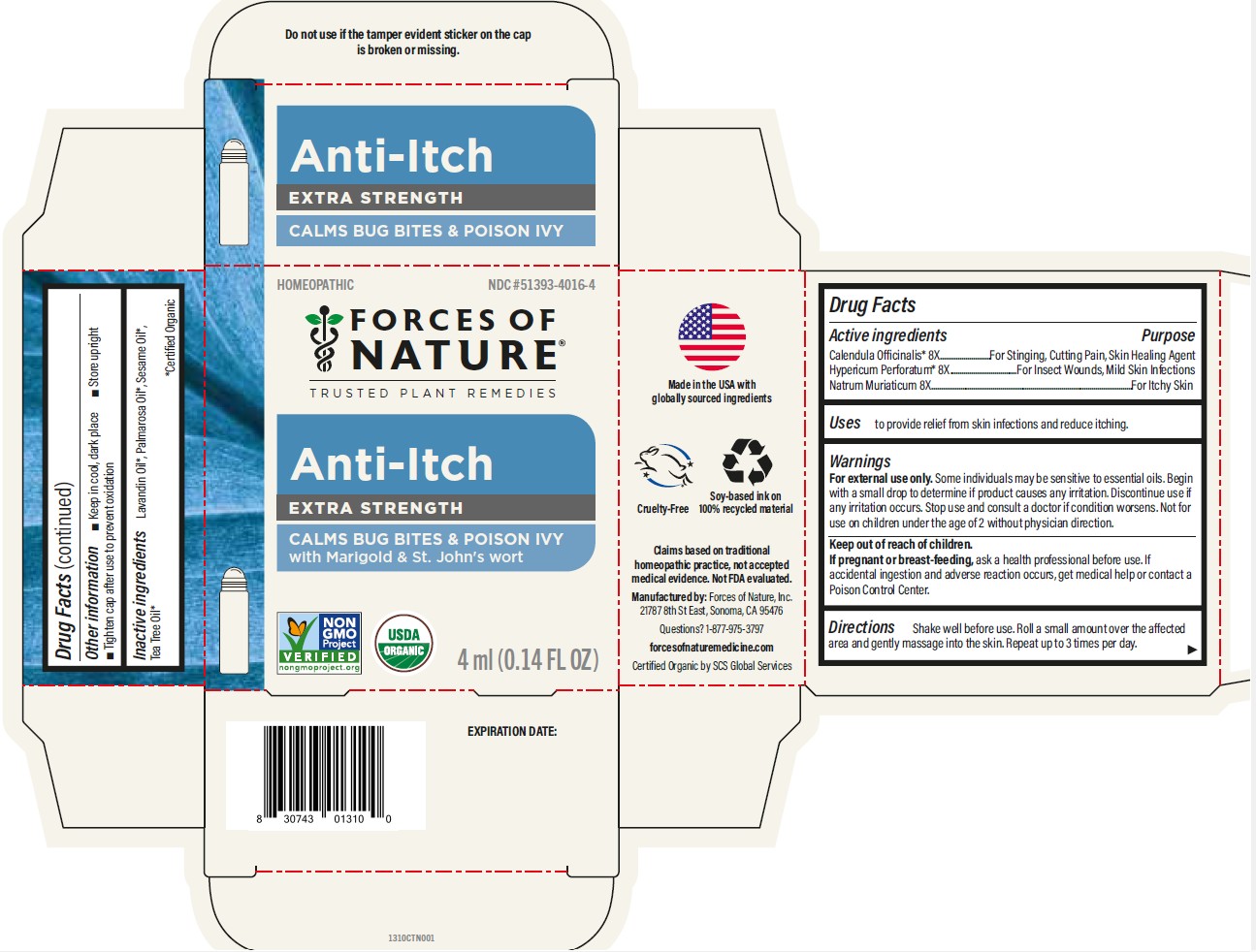 DRUG LABEL: Anti-Itch
NDC: 51393-4016 | Form: SOLUTION/ DROPS
Manufacturer: Forces of Nature
Category: homeopathic | Type: HUMAN OTC DRUG LABEL
Date: 20260225

ACTIVE INGREDIENTS: CALENDULA OFFICINALIS FLOWERING TOP 8 [hp_X]/100 mL; HYPERICUM PERFORATUM WHOLE 8 [hp_X]/100 mL; SODIUM CHLORIDE 8 [hp_X]/100 mL
INACTIVE INGREDIENTS: SESAME OIL; LAVANDIN OIL; TEA TREE OIL; PALMAROSA OIL

Anti-Itch
Extra Strength

Drug Facts

ACTIVE INGREDIENT

Active ingredients | Purpose
Calendula [USDA Certified Organic] 8X | For Stinging, Cutting Pain, Skin Healing Agent
Hypericum perforatum 8X | For Insect Wounds, Mild Skin Infections
Natrum muriaticum 8X | For Itchy Skin

Uses

to provide relief from skin infections and reduce itching.

Warnings

For external use only.Some individuals may be sensitive to essential oils. Begin with a small drop to determine if product causes any irritation. Discontinue use if any irritation occurs. Stop use and consult a doctor if condition worsens. Not for use on children under the age of 2 without physician direction.

Keep out of reach of children.

PREGNANCY OR BREAST FEEDING

If pregnant or breast-feeding,ask a health professional before use. If accidental ingestion and adverse reaction occurs, get medical help or contact a Poison Control Center.

Directions

shake well before use. Roll a small amount over the affected area and gently massage into the skin. Repeat up to three times per day.

Other information

- Keep in cool dark place
- store upright
- tighten cap after use to prevent oxidation

Inactive ingredients

Lavandin Oil*, Palmarosa Oil*, Sesame Oil*, Tea Tree Oil*

* Certified Organic

Questions or comments?

Questions? 1-877-975-3797

forcesofnaturemedicine.com

Manufactured by: Forces of Nature, Inc
21787 8th St East #3A Sonoma, CA 95476

RECENT MAJOR CHANGES

Minor adjustment to wording of Directions for Use to be more clear for users.

PRINCIPAL DISPLAY PANEL - 4 ml Bottle Carton

Homeopathic
NDC #51393-4016-4

FORCES OF NATURE®

TRUSTED PLANT REMEDIES

Anti-Itch

EXTRA STRENGTH

CALMS BUG BITES & POISON IVY

with Marigold & St. John's Wort

NON
GMO
Project
VERIFIED
nongmoproject.org

USDA

ORGANIC

4 ml (0.14 FL OZ)